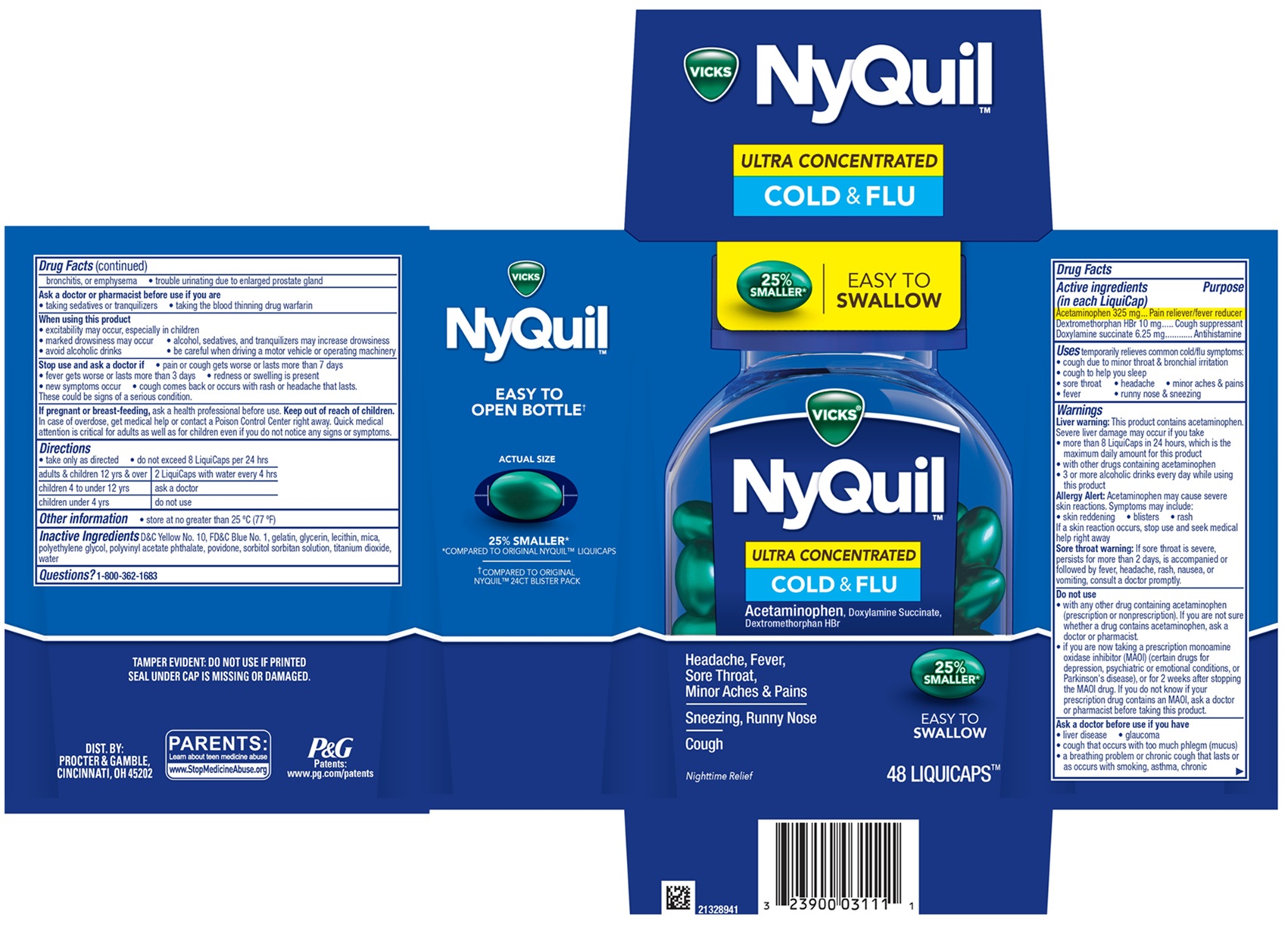 DRUG LABEL: Vicks NyQuil
NDC: 69423-801 | Form: CAPSULE, LIQUID FILLED
Manufacturer: The Procter & Gamble Manufacturing Company
Category: otc | Type: HUMAN OTC DRUG LABEL
Date: 20251202

ACTIVE INGREDIENTS: DOXYLAMINE SUCCINATE 6.25 mg/1 1; ACETAMINOPHEN 325 mg/1 1; DEXTROMETHORPHAN HYDROBROMIDE 10 mg/1 1
INACTIVE INGREDIENTS: MICA; GELATIN; SORBITOL; LECITHIN, SOYBEAN; POLYVINYL ACETATE PHTHALATE; PROPYLENE GLYCOL; POLYETHYLENE GLYCOL, UNSPECIFIED; FD&C BLUE NO. 1; GLYCERIN; WATER; TITANIUM DIOXIDE; POVIDONE; D&C YELLOW NO. 10

VICKS® NyQuil™ ULTRA CONCENTRATED COLD & FLU, LiquiCaps™

Drug Facts

Active ingredients (in each LiquiCap)

Acetaminophen 325 mg
Dextromethorphan HBr 10 mg
Doxylamine succinate 6.25 mg

Purpose

Pain reliever/fever reducer
Cough suppressant
Antihistamine

Uses

temporarily relieves common cold/flu symptoms:

• cough due to minor throat & bronchial irritation

• sore throat

• headache

• minor aches & pains

• fever

• runny nose & sneezing

Warnings

Liver warning:This product contains acetaminophen.
Severe liver damage may occur if you take
• more than 8 Liquicaps in 24 hours, which is the maximum daily amount for this product
• with other drugs containing acetaminophen
• 3 or more alcoholic drinks every day while using this product

Allergy Alert: Acetaminophen may cause severe skin reactions.

Symptoms may include:
• skin reddening • blisters • rash
If a skin reaction occurs, stop use and seek medical help right away

Sore throat warning:If sore throat is severe, persists for more than 2 days, is accompanied or followed by fever, headache, rash, nausea, or vomiting, consult a doctor promptly.

Do not use

• with any other drug containing acetaminophen (prescription or nonprescription). If you are not sure whether a drug contains acetaminophen, ask a doctor or pharmacist.
• if you are now taking a prescription monoamine oxidase inhibitor (MAOI) (certain drugs for depression, psychiatric or emotional conditions, or Parkinson's disease), or for 2 weeks after stopping the MAOI drug. If you do not know if your prescription drug contains an MAOI, ask a doctor or pharmacist before taking this product.

Ask a doctor before use if you have

• liver disease

• glaucoma

• cough that occurs with too much phlegm (mucus)

• a breathing problem or chronic cough that lasts or as occurs with smoking, asthma, chronic bronchitis, or emphysema

• trouble urinating due to enlarged prostate gland

Ask a doctor or pharmacist before use if you are

• taking sedatives or tranquilizers • taking the blood thinning drug warfarin

When using this product

• do not use more than directed

• excitability may occur, especially in children

• marked drowsiness may occur

• avoid alcoholic drinks

• be careful when driving a motor vehicle or operating machinery

• alcohol, sedatives, and tranquilizers may increase drowsiness

Stop use and ask a doctor if

• pain or cough gets worse or lasts more than 7 days

• fever gets worse or lasts more than 3 days

• redness or swelling is present

• new symptoms occur

• cough comes back or occurs with rash or headache that lasts.

These could be signs of a serious condition.

If pregnant or breast-feeding,

ask a health professional before use.

Keep out of reach of children.

OVERDOSAGE

In case of overdose, get medical help or contact a Poison Control Center right away. Quick medical attention is critical for adults as well as for children even if you do not notice any signs or symptoms.

Directions

- take only as directed
- do not exceed 8 LiquiCaps per 24 hrs

adults & children 12 yrs & over | 2 LiquiCaps with water every 4 hrs
children 4 to under 12 yrs | ask a doctor
children under 4 yrs | do not use

Other information

- store at no greater than 25° C

Inactive ingredients

Inactive Ingredients D&C Yellow No. 10, FD&C Blue No. 1, gelatin, glycerin, lecithin, mica, polyethylene glycol, polyvinyl acetate phthalate, povidone, sorbitol sorbitan solution, titanium dioxide, water

Questions?

1-800-362-1683

TAMPER EVIDENT: DO NOT USE IF PRINTED SEAL UNDER CAP IS MISSING OR DAMAGED.

DIST. BY PROCTER & GAMBLE,

CINCINNATI, OH 45202

PRINCIPAL DISPLAY PANEL - 48 LiquiCaps™

MAX STRENGTH

100% MORE LIQUICAPS†

VICKS®

NyQuil™

ULTRA CONCENTRATED

COLD & FLU

Acetaminophen, Doxylamine Succinate, Dextromethorphan HBr

Headache, Fever, Sore Throat, Minor Aches & Pains
Sneezing, Runny Nose
Cough

25% SMALLER*

EASY TO SWALLOW

Nighttime Relief

48 LIQUICAPS™